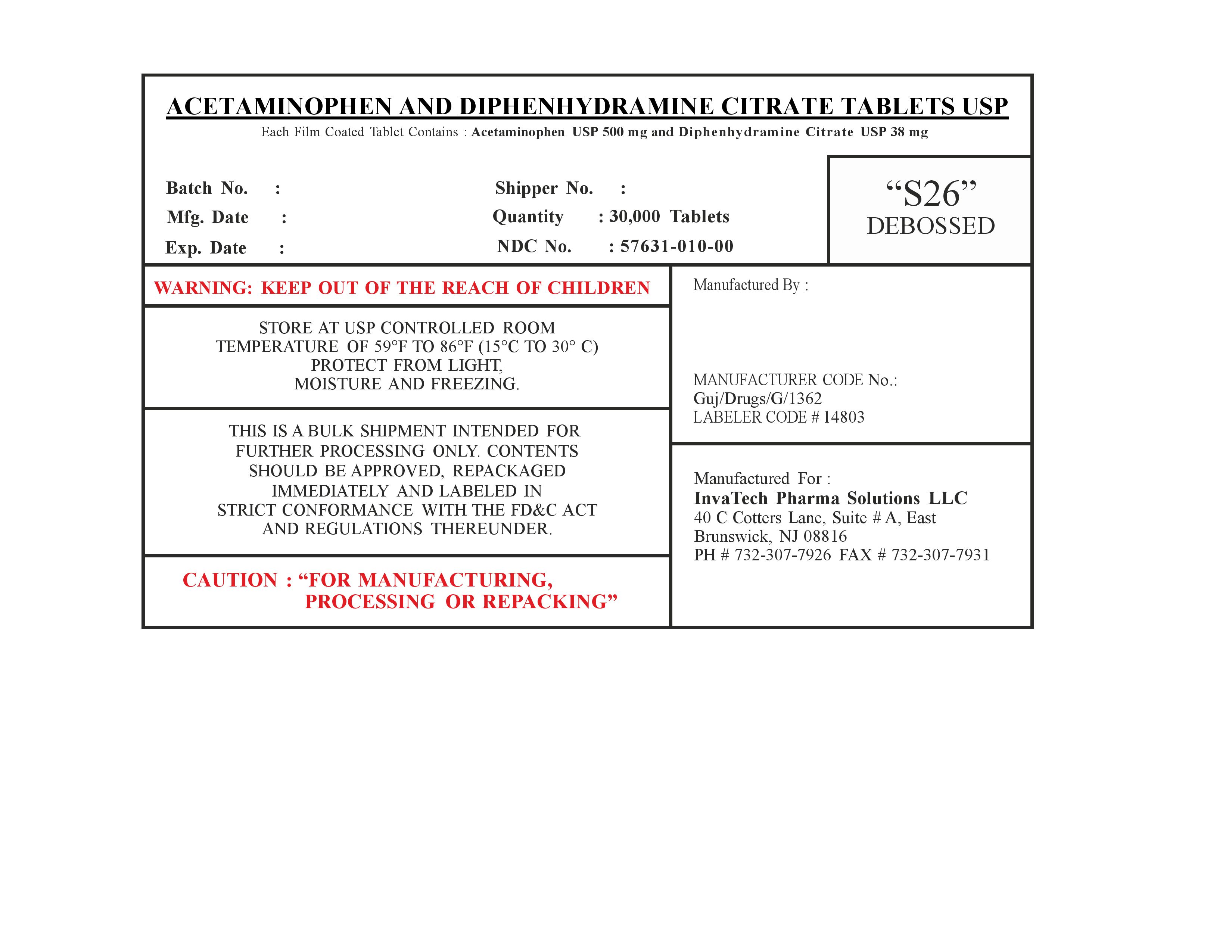 DRUG LABEL: Acetaminophen and Diphenhydramine citrate
NDC: 57631-010 | Form: TABLET
Manufacturer: InvaTech Pharma Solutions LLC
Category: otc | Type: HUMAN OTC DRUG LABEL
Date: 20251002

ACTIVE INGREDIENTS: ACETAMINOPHEN 500 mg/1 1; DIPHENHYDRAMINE CITRATE 38 mg/1 1
INACTIVE INGREDIENTS: HYPROMELLOSES; MAGNESIUM STEARATE; TITANIUM DIOXIDE; POLYETHYLENE GLYCOL 400; FD&C BLUE NO. 2; FD&C BLUE NO. 1; CELLULOSE, MICROCRYSTALLINE; STARCH, CORN; POVIDONE K30; SILICON DIOXIDE

Acetaminophen and Diphenhydramine citrate

KEEP OUT OF THE REACH OF CHILDREN

INDICATIONS AND USAGE

Analgesic and Antipyretic

DOSAGE AND ADMINISTRATION

FOR MANUFACTURING, PROCESSING OR REPACKING

WARNINGS

KEEP OUT OF THE REACH OF CHILDREN,REMOVE SILICA GEL BAG BEFORE USE

INACTIVE INGREDIENT

Microcrystalline Cellulose, Polyethylene glycol, Polyvinyl pyrrolidinone, Pregelatinized Starch, Starch, Stearic Acid powder, colloidal Silicon Dioxide, talc, Hypromellose

PURPOSE

FOR FURTHER MANUFACTURING, PROCESSING OR REPACKING